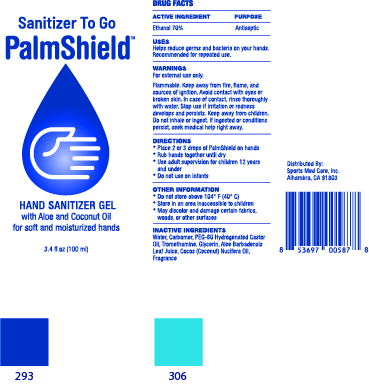 DRUG LABEL: PALM SHIELD HAND SANITIZER gel
NDC: 73793-0008 | Form: GEL
Manufacturer: SKINFARM	
Category: otc | Type: HUMAN OTC DRUG LABEL
Date: 20200903

ACTIVE INGREDIENTS: ALCOHOL 70 g/100 mL
INACTIVE INGREDIENTS: TROLAMINE; CARBOMER HOMOPOLYMER, UNSPECIFIED TYPE; GLYCERIN; WATER; ALOE VERA LEAF; COCONUT OIL; PEG-60 HYDROGENATED CASTOR OIL

Drug Facts

ACTIVE INGREDIENT

Alcohol

INACTIVE INGREDIENT

Water, Carbomer, PEG-60 Hytdrogenated Castor Oil, Trometharmine, Glycerin, Aloe Barbadensis Leaf Juice,Cocos (Coconut) Nucifera Oil, Fragrance

PURPOSE

Antiseptic

KEEP OUT OF REACH OF THE CHILDREN

INDICATIONS AND USAGE

For the external use only

WARNINGS

For external use only.

Flammable. Keep awau from fire, flame, and sources of ignition.

Avoid contact with eyes. If introduced to eyes, flush with water.
Do not ingest.
Discontinue use and contact a doctor if irritation and redness develops and
condition persist for more than 72 hours.
Keep out of reach of children. if swallowed, get medial help or contact a Poison Control Center right away

DOSAGE AND ADMINISTRATION

- Place 2 or 3 drops of PalmShield on hands
- Rub hands together until dry
- Use adult supervision for children 12 years
- May discolor and damage certain fabrics, woods, or other surfaces